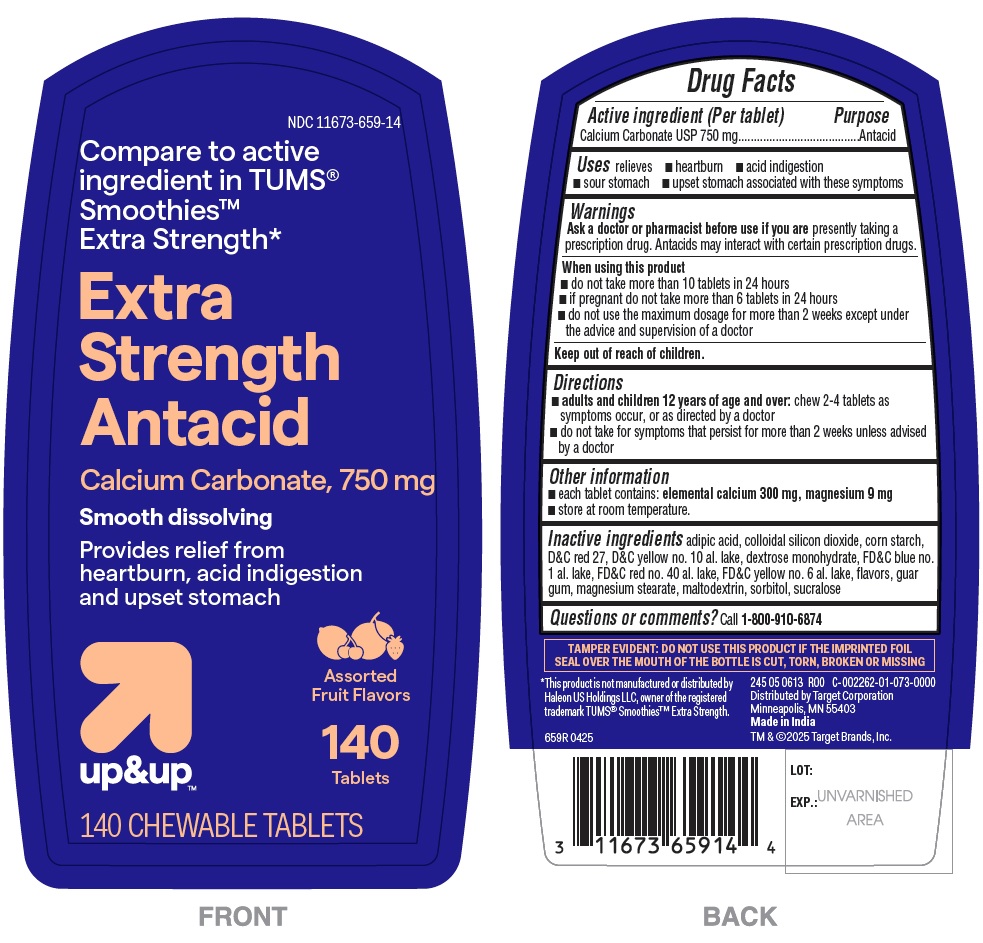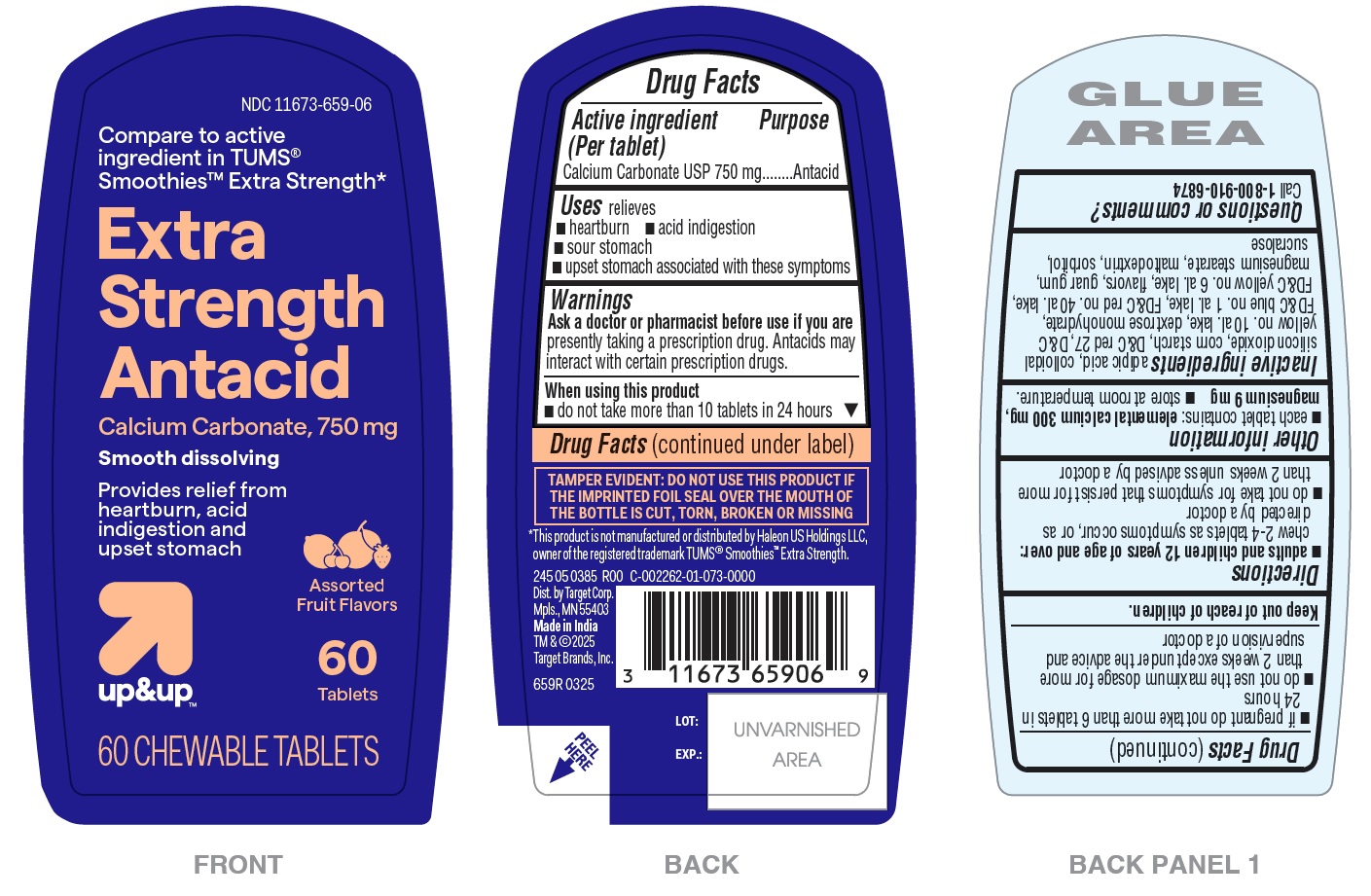 DRUG LABEL: Extra Strength Antacid Smooth Dissolving - Assorted Fruit
NDC: 11673-659 | Form: TABLET, CHEWABLE
Manufacturer: TARGET CORPORATION
Category: otc | Type: HUMAN OTC DRUG LABEL
Date: 20250405

ACTIVE INGREDIENTS: CALCIUM CARBONATE 750 mg/1 1
INACTIVE INGREDIENTS: STARCH, CORN; D&C YELLOW NO. 10 ALUMINUM LAKE; FD&C YELLOW NO. 6 ALUMINUM LAKE; DEXTROSE MONOHYDRATE; FD&C RED NO. 40 ALUMINUM LAKE; MALTODEXTRIN; SUCRALOSE; MAGNESIUM STEARATE; ADIPIC ACID; FD&C BLUE NO. 1 ALUMINUM LAKE; GUAR GUM; D&C RED NO. 27; SORBITOL; SILICON DIOXIDE

659R-Target-Calcium Carbonate 750mg Smooth dissolving chewable tablets- Assorted Fruits

Drug Facts

Active ingredient (in each tablet)

Calcium Carbonate USP 750 mg

Purpose

Antacid

INDICATIONS AND USAGE

Uses relieves

- heartburn
- acid indigestion
- sour stomach
- upset stomach associated with these symptoms

Warnings

Ask a doctor or pharmacist before use if you are presently taking a prescription drug. Antacids may interact with certain prescription drugs.

When using this product

- do not take more than 10 tablets in 24 hours
- if pregnant do not take more than 6 tablets in 24 hours
- do not use the maximum dosage for more than 2 weeks except under the advice and supervision of a doctor

Keep out of reach of children.

Directions

- adults and children 12 years of age and over: chew 2 – 4 tablets as symptoms occur, or as directed by a doctor
- do not take for symptoms that persist for more than 2 weeks unless advised by a doctor

Other information

- each tablet contains : elemental calcium 300 mg, magnesium 9 mg
- store at room temperature.

INACTIVE INGREDIENT

Inactive ingredients adipic acid, colloidal silicon dioxide, corn starch, D&C red 27, D&C yellow no. 10 al. lake, dextrose monohydrate, FD&C blue no. 1 al. lake, FD&C red no. 40 al. lake, FD&C yellow no. 6 al. lake, flavors, guar gum, magnesium stearate, maltodextrin, sorbitol, sucralose

Questions or comments? Call 1-800-910-6874